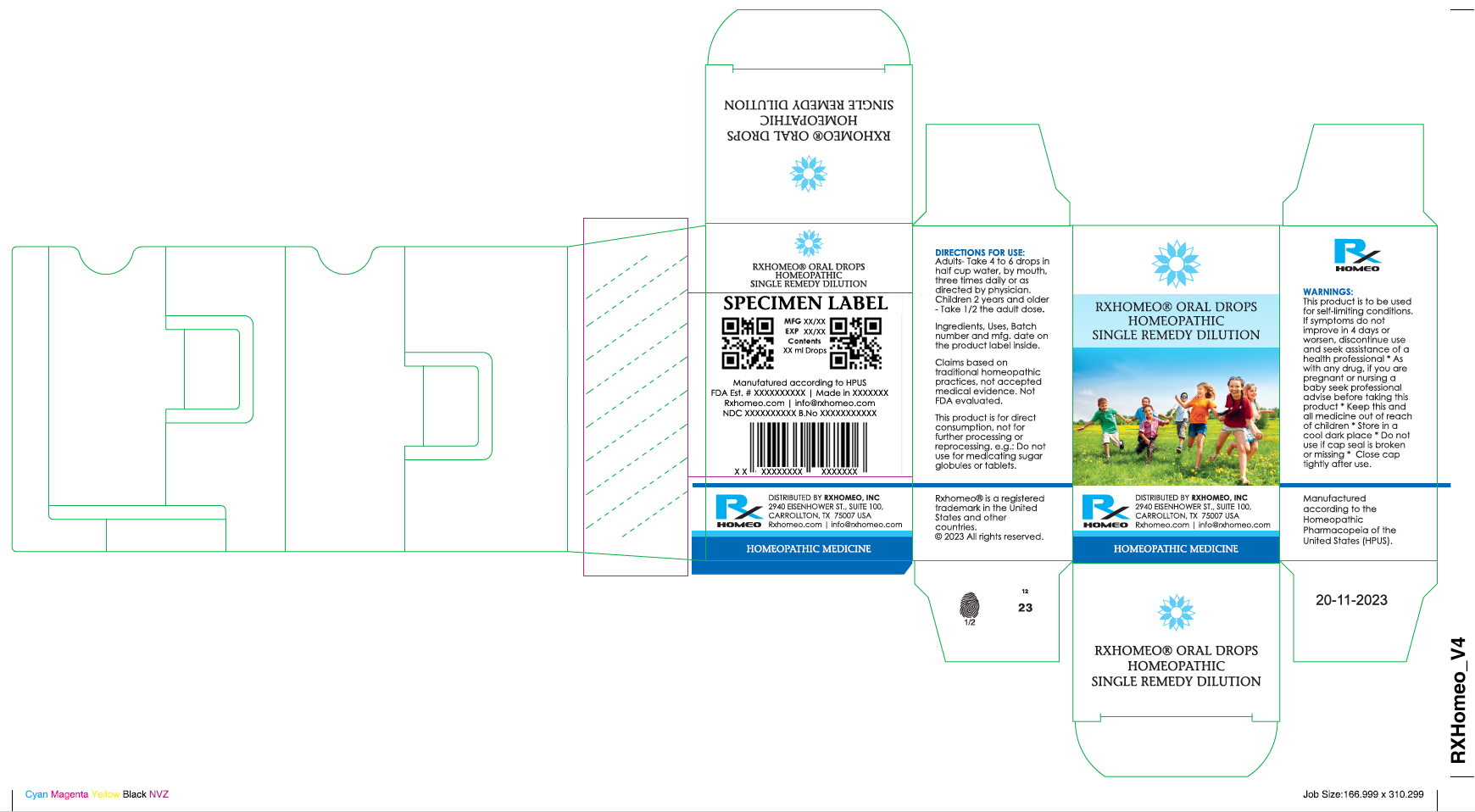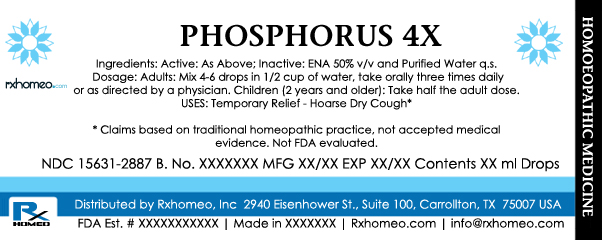 DRUG LABEL: PHOSPHORUS
NDC: 15631-2887 | Form: LIQUID
Manufacturer: Rxhomeo Private Limited d.b.a. Rxhomeo, Inc
Category: homeopathic | Type: HUMAN OTC DRUG LABEL
Date: 20240607

ACTIVE INGREDIENTS: PHOSPHORUS 4 [hp_X]/1 mL
INACTIVE INGREDIENTS: ALCOHOL; WATER

ACTIVE INGREDIENT

PHOSPHORUS HPUS 4X and higher

USES

USES: Temporary Relief - Hoarse Dry Cough*

* Claims based on traditional homeopathic practice, not accepted medical evidence. Not FDA evaluated.

INDICATIONS

Condition listed above or as directed by the physician

DOSAGE

Adults: Mix 4-6 drops in 1/2 cup of water, take orally three times daily or as directed by a physician. Children (2 years and older): Take half the adult dose.

WARNINGS

This product is to be used for self-limiting conditions

STOP USE

If symptoms do not improve in 4 days, or worsen, discontinue use and seek assistance of health professional

PREGNANCY OR BREAST FEEDING

As with any drug, if you are pregnant, or nursing a baby, seek professional advice before taking this product

KEEP OUT OF REACH OF CHILDREN

Keep this and all medication out of reach of children

Do not use if capseal is broken or missing.

Close the cap tightly after use.

INACTIVE INGREDIENTS

Active: As Above; Inactive: ENA 50% v/v and Purified Water q.s.

STORAGE

Store in a cool dark place

QUESTIONS OR COMMENTS

www.Rxhomeo.com | 1.888.2796642 | info@rxhomeo.com - Rxhomeo, Inc 2940 Eisenhower St., Suite 100, Carrollton, TX 75007 USA